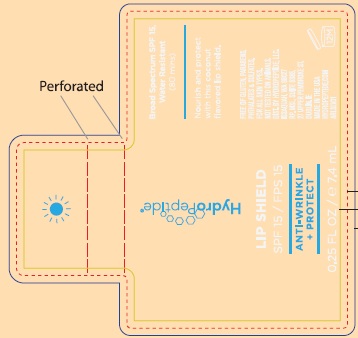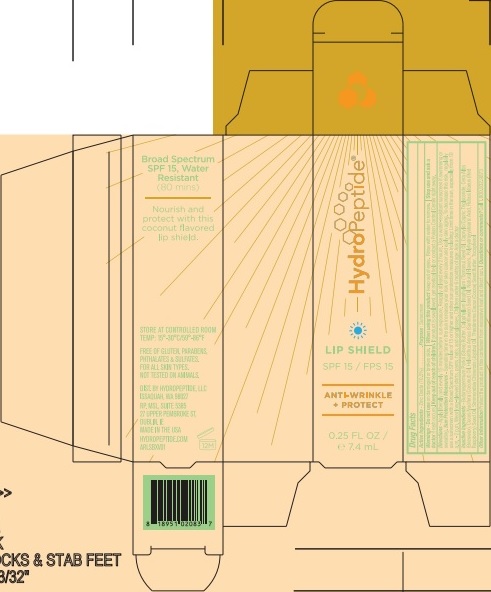 DRUG LABEL: LIP BALM
NDC: 62932-187 | Form: STICK
Manufacturer: Private Label Select Ltd CO
Category: otc | Type: HUMAN OTC DRUG LABEL
Date: 20181130

ACTIVE INGREDIENTS: ZINC OXIDE 20 g/100 g
INACTIVE INGREDIENTS: SUNFLOWER OIL; HELIANTHUS ANNUUS SEED WAX; YELLOW WAX; COCONUT OIL; SHEA BUTTER; CAPRYLIC/CAPRIC/LINOLEIC TRIGLYCERIDE; SIMMONDSIA CHINENSIS SEED WAX; TAMANU OIL; RASPBERRY SEED OIL; TOCOPHEROL; COCOA BUTTER

HydroPeptide Lip Shield SPF15